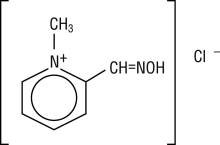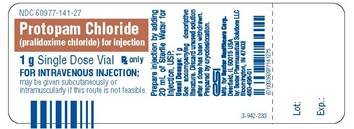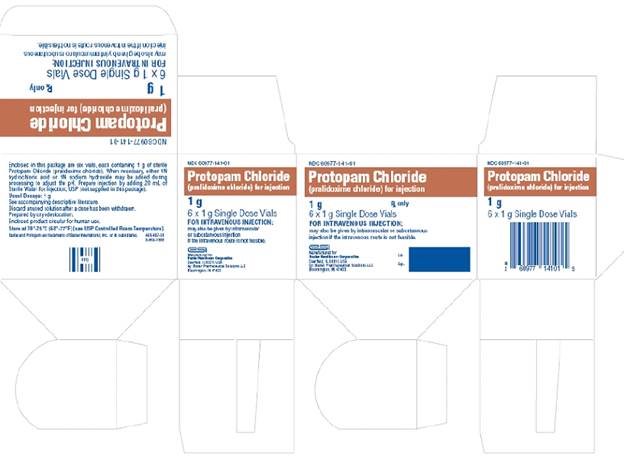 DRUG LABEL: Protopam Chloride
NDC: 60977-141 | Form: INJECTION, POWDER, LYOPHILIZED, FOR SOLUTION
Manufacturer: Baxter Healthcare Corporation
Category: prescription | Type: HUMAN PRESCRIPTION DRUG LABEL
Date: 20180101

ACTIVE INGREDIENTS: PRALIDOXIME CHLORIDE 1 g/20 mL
INACTIVE INGREDIENTS: SODIUM HYDROXIDE

PROTOPAM (pralidoxime chloride) for Injection

DESCRIPTION

Chemical name: 2-formyl-1-methylpyridinium chloride oxime. Available in the United States as PROTOPAM Chloride for Injection (PROTOPAM Chloride), pralidoxime chloride is frequently referred to as 2-PAM Chloride.

Structural formula:

C7H9CIN2O M.W. 172.61

Pralidoxime chloride occurs as an odorless, white, nonhygroscopic, crystalline powder which is soluble in water. Stable in air, it melts between 215º and 225º C, with decomposition.

The specific activity of the drug resides in the 2-formyl-1-methylpyridinium ion and is independent of the particular salt employed. The chloride is preferred because of physiologic compatibility, excellent water solubility at all temperatures, and high potency per gram, due to its low molecular weight.

Pralidoxime chloride is a cholinesterase reactivator.

PROTOPAM Chloride for intravenous injection or infusion is prepared by cryo-desiccation. Each vial contains 1000 mg of sterile pralidoxime chloride, and sodium hydroxide to adjust pH, to be reconstituted with 20 mL of Sterile Water for Injection, USP. The pH of the reconstituted solution is 3.5 to 4.5. Intramuscular or subcutaneous injection may be used when intravenous injection is not feasible.

CLINICAL PHARMACOLOGY

The principal action of pralidoxime chloride is to reactivate cholinesterase (mainly outside of the central nervous system) which has been inactivated by phosphorylation due to an organophosphate pesticide or related compound. The destruction of accumulated acetylcholine can then proceed, and neuromuscular junctions will again function normally. Pralidoxime chloride also slows the process of “aging” of phosphorylated cholinesterase to a nonreactivatable form, and detoxifies certain organophosphates by direct chemical reaction. The drug has its most critical effect in relieving paralysis of the muscles of respiration. Because pralidoxime chloride is less effective in relieving depression of the respiratory center, atropine is always required concomitantly to block the effect of accumulated acetylcholine at this site. Pralidoxime chloride relieves muscarinic signs and symptoms, salivation, bronchospasm, etc., but this action is relatively unimportant since atropine is adequate for this purpose.

PROTOPAM Chloride has been studied in animals as an antidote against numerous organophosphate pesticides, chemicals, and drugs (see Animal Pharmacology and Toxicology). Regardless of whether or not animal studies suggest that the organophosphate poison to which a particular patient has been exposed is amenable to treatment with pralidoxime chloride, the use of pralidoxime chloride should, nevertheless, be considered in any life-threatening situation resulting from poisoning by these compounds, since the limited and arbitrary conditions of pharmacologic screening do not always accurately reflect the usefulness of pralidoxime chloride in the clinical situation.

CLINICAL STUDIES

There are no adequate and well controlled clinical studies that establish the effectiveness of pralidoxime chloride as a treatment for poisoning with organophosphates having anticholinesterase activity. However, its use has been considered to be successful against poisoning with numerous pesticides, chemicals, and drugs.

Pharmacokinetics

Animal studies suggest that the minimum therapeutic concentration of pralidoxime in plasma is 4 µg/mL; this level is reached in about 16 minutes after a single injection of 600 mg pralidoxime chloride. In one study of healthy adult volunteers and patients self-poisoned with organophosphate compounds, a single intramuscular injection of 1000 mg of pralidoxime chloride resulted in mean peak plasma levels of 7.5 ± 1.7 µg/mL and 9.9 ± 2.4 µg/mL, respectively. Time to reach the mean peak plasma levels in both groups was similar, 34 minutes in healthy adults and 33 minutes in poisoned patients. Mean half-life was about 3 hours in both groups.

Some evidence suggests that a loading dose followed by continuous intravenous infusion of pralidoxime chloride may maintain therapeutic levels longer than short intermittent infusion therapy. In a cross-over study of seven healthy adults (18 – 50 years) a short intravenous infusion dose of 16 mg/kg over 30 minutes was compared to an intravenous loading dose of 4 mg/kg over 15 minutes, followed by 3.2 mg/kg/hr for 3.75 hours (for a total dose of 16 mg/kg). Results showed that the mean time over which plasma levels were maintained above 4 µg/mL was prolonged in the volunteers who received a loading dose followed by continuous infusion as compared to those who received short infusion therapy (257.5 ± 50.5 min vs. 118.0 ± 52.1 min). Use of continuous intravenous infusion in adult patients with organophosphate poisoning has been described in several case reports, with and without loading doses. Infusion rates ranged from 400 – 600 mg/hr. In one case the blood levels were 11.6 – 13.7 µg /mL when given 400 mg/hr over 5 days (measured at 5, 10 and 18 hours). In another case following an initial loading dose of 1000 mg, blood levels were 11.79 µg/mL when given 500 mg/hr and 17.26 µg/mL when given 600 mg/hr. In the latter case the pralidoxime elimination half-life was 4 hours. In two other cases blood levels were not measured.

Pralidoxime chloride is distributed throughout the extracellular water; its apparent volume of distribution at steady state has been reported to range from 0.60 to 2.7 L/kg. Pralidoxime chloride is not bound to plasma protein.

Pralidoxime chloride is relatively short acting and repeated doses may be needed, unless continuous intravenous infusion is selected. Simulations suggest that after a dose of 1000 mg given intravenously, concentrations fall below 4 µg/mL in about 1.5 hours. The short duration of action of pralidoxime chloride and the necessity for repeated doses should be considered especially where there is any evidence of continuing absorption of the poison. The apparent half-life of pralidoxime chloride is 74 to 77 minutes. The drug is rapidly excreted in the urine by renal tubular secretion, partly unchanged, and partly as a metabolite produced by the liver. After intramuscular administration of 1000 mg of pralidoxime chloride, the renal clearance has been reported to be 7.2 ± 2.9 mL/min/kg in healthy volunteers and 3.6 ± 1.5 mL/min/kg in organophosphate-poisoned patients.

In one study of 11 organophosphate-poisoned pediatric patients (age, 0.8 to 18 years), an intravenous loading dose of 15-50 mg/kg (mean 29 mg/kg) of pralidoxime chloride followed by a continuous infusion of 10-16 mg/kg/hr (mean 14 mg/kg/hr) over 12 to 43 hours (mean 27 ± 8 hours) resulted in an average steady state plasma concentration of 22.2 mg/L (6.9 to 47.4 mg/L) and an average body clearance of 0.88 L/kg/hr (0.28 to 2.20 L/kg/hr). After the continuous infusion was discontinued, determinations of the apparent volume of distribution and half-life ranged from 1.7 to 13.8 L/kg and from 2.4 to 5.3 hours, respectively.

INDICATIONS AND USAGE

PROTOPAM Chloride is indicated as an antidote:

1. In the treatment of poisoning due to those pesticides and chemicals (e.g., nerve agents) of the organophosphate class which have anticholinesterase activity and
2. In the control of overdosage by anticholinesterase drugs used in the treatment of myasthenia gravis.

The principal indications for the use of PROTOPAM Chloride are muscle weakness and respiratory depression. In severe poisoning, respiratory depression may be due to muscle weakness.

CONTRAINDICATIONS

There are no known absolute contraindications for the use of PROTOPAM Chloride (see PRECAUTIONS, Drug Interactions and DOSAGE AND ADMINISTRATION). Relative contraindications include known hypersensitivity to the drug and other situations in which the risk of its use clearly outweighs possible benefit.

WARNINGS

PROTOPAM Chloride is not effective in the treatment of poisoning due to phosphorus, inorganic phosphates, or organophosphates not having anticholinesterase activity.

PROTOPAM Chloride is not indicated as an antidote for intoxication by pesticides of the carbamate class since it may increase the toxicity of carbaryl.

PRECAUTIONS

General

PROTOPAM Chloride has been well tolerated in most cases, but it must be remembered that the desperate condition of the organophosphate-poisoned patient will generally mask such minor signs and symptoms as have been noted in normal subjects.

Intravenous administration of PROTOPAM Chloride should be carried out slowly and, preferably, by continuous or intermittent infusion, since temporary worsening of cholinergic manifestations (i.e. tachycardia, cardiac arrest, laryngospasm, and muscle rigidity or paralysis) may occur if PROTOPAM Chloride is infused too rapidly. The intermittent infusion rate should not exceed 200 mg/minute. If intravenous administration is not feasible, intramuscular or subcutaneous injection should be used (see DOSAGE AND ADMINISTRATION).

PROTOPAM Chloride should be used with great caution in treating organophosphate overdosage in cases of myasthenia gravis since it may precipitate a myasthenic crisis.

Because pralidoxime is excreted in the urine, a decrease in renal function will result in increased blood levels of the drug. Thus, the dosage of PROTOPAM Chloride should be reduced in the presence of renal insufficiency.

Laboratory Tests

Treatment of organophosphate poisoning should be instituted without waiting for the results of laboratory tests. Red blood cell, plasma cholinesterase, and urinary paranitrophenol measurements (in the case of parathion exposure) may be helpful in confirming the diagnosis and following the course of the illness, although such tests may be normal in the face of clinically significant organophosphate poisoning. A reduction in red blood cell cholinesterase concentration to below 50% of normal has been seen only with organophosphate ester poisoning.

Drug Interactions

When atropine and pralidoxime chloride are used together, the signs of atropinization (flushing, mydriasis, tachycardia, dryness of the mouth and nose) may occur earlier than might be expected when atropine is used alone. This is especially true if the total dose of atropine has been large and the administration of pralidoxime chloride has been delayed.

The following precautions should be kept in mind in the treatment of anticholinesterase poisoning, although they do not bear directly on the use of pralidoxime chloride: since barbiturates are potentiated by the anticholinesterases, they should be used cautiously in the treatment of convulsions; morphine, theophylline, aminophylline, reserpine, and phenothiazine-type tranquilizers should be avoided in patients with organophosphate poisoning. Prolonged paralysis has been reported in patients when succinylcholine is given with drugs having anticholinesterase activity; therefore, it should be used with caution.

Carcinogenesis, Mutagenesis, Impairment of Fertility

Because pralidoxime chloride is indicated for short-term emergency use only, no investigations of its potential for carcinogenesis, mutagenesis, or impairment of fertility have been conducted by the manufacturer, or reported in the literature.

Pregnancy

Teratogenic Effects:

Animal reproduction studies have not been conducted with pralidoxime chloride. It is also not known whether pralidoxime chloride can cause fetal harm when administered to a pregnant woman or can affect reproduction capacity. Pralidoxime chloride should be given to a pregnant woman only if clearly needed.

Nursing Mothers

It is not known whether this drug is excreted in human milk. Because many drugs are excreted in human milk, caution should be exercised when pralidoxime chloride is administered to a nursing woman.

Pediatric Use

There are no adequate and well-controlled clinical trials that establish the effectiveness of pralidoxime chloride in pediatric patients. Efficacy has been extrapolated from the adult population and is supported by nonclinical studies, pharmacokinetic studies in adults and experience in the pediatric population (see DOSAGE AND ADMINISTRATION). As in adults, laryngospasm, cardiac arrest, tachycardia, and muscle rigidity or paralysis have been reported following rapid intravenous injection. Muscle fasciculations, apnea, and convulsions have also been reported.

Geriatric Use

Clinical studies of PROTOPAM Chloride did not include sufficient numbers of subjects aged 65 and over to determine whether they respond differently from younger subjects. Other reported clinical experience has not identified differences in responses between the elderly and younger patients. In general, dose selection for an elderly patient should be cautious, usually starting at the low end of the dosing range, reflecting the greater frequency of decreased hepatic, renal, or cardiac function, and of concomitant disease or other drug therapy.

ADVERSE REACTIONS

Forty to 60 minutes after intramuscular injection, mild to moderate pain may be experienced at the site of injection.

Pralidoxime chloride may cause blurred vision, diplopia and impaired accommodation, dizziness, headache, drowsiness, nausea, tachycardia, increased systolic and diastolic blood pressure, hyperventilation, and muscular weakness when given parenterally to normal volunteers who have not been exposed to anticholinesterase poisons. In patients, it is very difficult to differentiate the toxic effects produced by atropine or the organophosphate compounds from those of the drug.

Elevations in SGOT and/or SGPT enzyme levels were observed in 1 of 6 normal volunteers given 1200 mg of pralidoxime chloride intramuscularly, and in 4 of 6 volunteers given 1800 mg intramuscularly. Levels returned to normal in about 2 weeks. Transient elevations in creatine phosphokinase were observed in all normal volunteers given the drug.

When atropine and pralidoxime chloride are used together, the signs of atropinization may occur earlier than might be expected when atropine is used alone. This is especially true if the total dose of atropine has been large and the administration of pralidoxime chloride has been delayed. Excitement and manic behavior immediately following recovery of consciousness have been reported in several cases. However, similar behavior has occurred in cases of organophosphate poisoning that were not treated with pralidoxime chloride.

DRUG ABUSE AND DEPENDENCE

PROTOPAM Chloride is not subject to abuse and possesses no known potential for dependence.

OVERDOSAGE

Manifestations of Overdosage

Observed in normal subjects only: dizziness, blurred vision, diplopia, headache, impaired accommodation, nausea, slight tachycardia. In therapy, it has been difficult to differentiate side effects due to the drug from those due to the effects of the poison.

DOSAGE AND ADMINISTRATION

Organophosphate Poisoning

Treatment should include general supportive care, atropinization, and decontamination, in addition to the use of PROTOPAM Chloride. Treatment is most effective if initiated immediately after poisoning. Administration of PROTOPAM Chloride should be carried out slowly and, preferably, by infusion. If intravenous administration is not feasible, intramuscular or subcutaneous injection should be used. Generally, little is accomplished if PROTOPAM Chloride is given more than 36 hours after termination of exposure to the poison. When the poison has been ingested, it is particularly important to take into account the likelihood of continuing absorption from the lower bowel since this constitutes new exposure and fatal relapses have been reported after initial improvement. In such cases, additional doses of PROTOPAM Chloride may be needed every three to eight hours. In effect, the patient should be “titrated” with PROTOPAM Chloride as long as signs of poisoning recur. As in all cases of organophosphate poisoning, care should be taken to keep the patient under observation for at least 48 to 72 hours.

If dermal exposure has occurred, clothing should be removed and the hair and skin washed thoroughly with sodium bicarbonate or alcohol as soon as possible.

Supportive care, including airway management, respiratory and cardiovascular support, correction of metabolic abnormalities, and seizure control, may be necessary in cases of severe organophosphate poisoning.

Atropine should be given as soon as possible after hypoxemia is improved. Atropine should not be given in the presence of significant hypoxia due to the risk of atropine-induced ventricular fibrillation. In adults, atropine may be given intravenously in doses of 2 to 4 mg. This should be repeated at 5- to 10-minute intervals until full atropinization (secretions are inhibited) or signs of atropine toxicity appear (delirium, hyperthermia, muscle twitching).

Some degree of atropinization should be maintained for at least 48 hours, and until any depressed blood cholinesterase activity is reversed.

Use of morphine, theophylline, aminophylline, reserpine, and phenothiazine-type tranquilizers should be avoided in patients with organophosphate poisoning (see PRECAUTIONS, Drug Interactions). Prolonged paralysis has been reported in patients when succinylcholine is given with drugs having anticholinesterase activity; therefore, it should be used with caution.

After the effects of atropine become apparent, PROTOPAM Chloride may be administered.

Symptoms Of Nerve Agent And Insecticide Poisoning

PROTOPAM Chloride dosing is based, in part, on the severity of symptoms of nerve agent intoxication. These symptoms include the following:

MILD symptoms:

1. Blurred vision and sore eyes
2. Teary eyes*
3. Runny nose*
4. Increased salivation such as sudden drooling*
5. Chest tightness or difficulty breathing
6. Tremors throughout the body or muscular twitching
7. Nausea and vomiting
8. Involuntary respiratory secretions

SEVERE symptoms:

1. Strange or confused behavior
2. Severe difficulty breathing or respiratory secretions
3. Severe muscular twitching and general weakness**
4. Involuntary urination and defecation*
5. Convulsions
6. Unconsciousness

Symptoms in INFANTS AND YOUNG CHILDREN:

* These symptoms are sometimes observed in healthy infants and young children. In this age group, these symptoms are less reliable than other symptoms listed. Symptoms must be considered collectively when nerve agent or pesticide exposure is known or suspected.

** Infants may become drowsy or unconscious, with muscle floppiness rather than muscle twitching, soon after exposure to nerve agents or pesticides.

ADULT DOSING

ADULT INTRAVENOUS DOSING:

Refer to the Preparation for Administration section for instructions on reconstitution and dilution of PROTOPAM Chloride that result in a 10-20 mg/mL solution for intravenous infusion.

Inject an initial dose of 1000 to 2000 mg of PROTOPAM Chloride, preferably as an infusion in 100 mL of normal saline, over a 15- to 30-minute period. If this is not practical or if pulmonary edema is present, the dose should be given slowly (over not less than five minutes) by intravenous injection, as a 50 mg/mL solution in water (e.g., 1000 mg in 20 mL). A second dose of 1000 to 2000 mg may be indicated after about one hour if muscle weakness has not been relieved. Additional doses may be given every 10-12 hours if muscle weakness persists.

Intravenous administration of PROTOPAM Chloride should be carried out slowly and, preferably, by continuous or intermittent infusion, since temporary worsening of cholinergic manifestations (i.e. tachycardia, cardiac arrest, laryngospasm, and muscle rigidity or paralysis) may occur if PROTOPAM Chloride is infused too rapidly. The intermittent infusion rate should not exceed 200 mg/minute. If intravenous administration is not feasible, intramuscular or subcutaneous injection should be used.

Evidence suggests that a loading dose followed by continuous intravenous infusion of PROTOPAM Chloride may maintain therapeutic levels longer than traditional short intermittent infusions therapy (see Pharmacokinetics).

ADULT INTRAMUSCULAR DOSING:

Refer to the Preparation for Administration section for instructions on reconstitution of PROTOPAM Chloride that result in an approximate 300 mg/mL solution for intramuscular administration.

Intramuscular dosing in adults should be based on the severity of clinical symptoms.

MILD SYMPTOMS

1. For treatment of mild symptoms, administer a 600 mg (2 mL) intramuscular dose of PROTOPAM Chloride. Wait 15 minutes for PROTOPAM Chloride to take effect.
2. If, after 15 minutes, mild symptoms persist, then administer a second 600 mg (2 mL) intramuscular dose of PROTOPAM Chloride.
3. If, after an additional 15 minutes, mild symptoms continue to persist, a third 600 mg (2 mL) dose of PROTOPAM Chloride may be administered for a total cumulative dose of 1800 mg.
4. If at any time after the first dose, the patient develops severe symptoms, administer two additional 600 mg intramuscular doses in rapid succession for a total cumulative dose of 1800 mg of PROTOPAM Chloride.

SEVERE SYMPTOMS

1. For treatment of severe symptoms, administer three 600 mg intramuscular doses (3 doses of 2 mL each) in rapid succession for a total dose of 1800 mg of PROTOPAM Chloride.

PERSISTENT SYMPTOMS

1. If symptoms persist after administering the complete 1800 mg regimen (3 injections of 600 mg each), the series may be repeated beginning approximately 1 hour after administration of the last injection.

PEDIATRIC DOSING (FOR PATIENTS 16 YEARS AND UNDER)

PEDIATRIC INTRAVENOUS DOSING:

Refer to the Preparation for Administration section for instructions on reconstitution and dilution of PROTOPAM Chloride that result in 10-20 mg/mL solution for intravenous infusion.

PROTOPAM Chloride can be given as intermittent intravenous infusions or as a loading dose followed by continuous intravenous infusion, depending upon the patient’s clinical condition. The specific dose given should depend upon the severity of the symptoms.

Loading Dose Following By Continuous Infusion:

Administer a loading dose of 20-50 mg/kg (not to exceed 2000 mg/dose) over 15-30 minutes followed by a continuous infusion of 10-20 mg/kg/hour.

Intermittent Infusion Dosing:

Administer an initial intermittent infusion of 20-50 mg/kg (not to exceed 2000 mg/dose) over 15-30 minutes. A second dose of 20-50 mg/kg may be indicated after about one hour if muscle weakness has not been relieved. Repeat dosing is permissible every 10-12 hours as needed.

If it is not practical to administer intermittent or continuous intravenous infusions, or if pulmonary edema is present, the 20-50 mg/kg dose should be given slowly (over not less than five minutes) by intravenous injection as a 50 mg/mL solution in water (see Preparation for Administration section). Additional doses may be given every 10-12 hours if muscle weakness persists.

PEDIATRIC INTRAMUSCULAR DOSING:

Refer to the Preparation for Administration section for instructions on reconstitution of PROTOPAM Chloride that result in an approximate 300 mg/mL solution for intramuscular administration.

Intramuscular injections in children should be administered in the anterolateral aspect of the thigh to avoid the nerve, artery and vein, as well as the femur.

Pharmacokinetic modeling using published data from the scientific literature was conducted to derive intramuscular dosing recommendations in the pediatric population. The specific intramuscular dose of PROTOPAM Chloride should depend upon the severity of the symptoms.

MILD SYMPTOMS

1. For the treatment of mild symptoms, administer a weight-appropriate intramuscular dose (see Table 1 below) of PROTOPAM Chloride. Wait 15 minutes for PROTOPAM Chloride to take effect.
2. If, after 15 minutes, mild symptoms persist, then administer a second weight-appropriate intramuscular dose of PROTOPAM Chloride.
3. If after an additional 15 minutes, mild symptoms continue to persist, a third weight-appropriate intramuscular dose of PROTOPAM Chloride may be administered.
4. The three PROTOPAM Chloride injections together are considered a single course of treatment, and the total amount of PROTOPAM Chloride administered per course of treatment (i.e., 3 weight-appropriate injections) should not exceed the total amounts listed in Table 1 below.
5. If at any time after the first dose, the patient develops severe symptoms, administer two additional weight-appropriate intramuscular doses of PROTOPAM Chloride in rapid succession.

SEVERE SYMPTOMS

1. For treatment of severe symptoms, administer the weight-appropriate intramuscular dose (see Table 1 below) of PROTOPAM Chloride Injection as three injections, in rapid succession, into the patient’s anterolateral thigh (see Table 1 below).

PERSISTENT SYMPTOMS

1. If symptoms persist after administering a complete course (3 injections of the weight-appropriate dose each), the series may be repeated beginning approximately 1 hour after administration of the last injection.

Table 1: Pediatric Intramuscular Dosing Recommendations [Dosing is based on an approximate 300 mg/mL solution.]
Weight in kg | Dose Per Injection [During the treatment of mild symptoms, if at any time after the first dose, the patient develops severe symptoms, administer two additional weight-appropriate intramuscular doses of PROTOPAM Chloride in rapid succession.] | Total Dose per Three-Injection Course [Additional courses of PROTOPAM Chloride may be administered beginning one hour after the last injection. A single course consists of three separate, weight-appropriate injections, administered either with 15 minute inter-injection observation periods for patients with mild symptoms, or all in rapid succession for patients with severe symptoms.]
< 40kg | 15 mg/kg | 45 mg/kg
≥ 40 kg [Weight of 40 kg corresponds to approximately the 50th percentile for a 12 year old child per the weight-for-age percentile growth charts published by the Centers for Disease Control and Prevention in 2000.] | Use Adult Dosing Recommendations [Adult Dose Per Injection is 600 mg; Total Adult Dose per Three-Injection Course is 1800 mg.] | Use Adult Dosing Recommendations

Anticholinesterase Overdosage

As an antagonist to such anticholinesterases as neostigmine, pyridostigmine, and ambenonium, which are used in the treatment of myasthenia gravis, PROTOPAM Chloride may be given in a dosage of 1000 to 2000 mg intravenously followed by increments of 250 mg every five minutes.

Preparation for Administration

PROTOPAM Chloride is supplied as 1000 mg single-dose vials for injection.

For INTRAVENOUS infusion: Reconstitute a single PROTOPAM Chloride 1000 mg vial by adding 20 mL of Sterile Water for Injection, USP, which results in a 50 mg/mL concentration.

The solution should further be diluted with Normal Saline for Injection, USP to achieve a concentration of 10 to 20 mg/mL (e.g. 1000 mg in 100 mL or 2000 mg in 100 mL).

For fluid restricted patients or for rapid administration (over at least 5 min), a maximum concentration of 50 mg/mL may be used.

For INTRAMUSCULAR injection: Reconstitute a single PROTOPAM Chloride 1000 mg vial by adding 3.3 mL of Sterile Water for Injection, USP for an approximate concentration of 300 mg/mL.

Parenteral drug products should be inspected visually for particulate matter and discoloration prior to administration, whenever solution and container permit.

Discard unused solution after a dose has been withdrawn.

HOW SUPPLIED

NDC 60977-141-01—Hospital Package: This contains six 20 mL vials of 1 g each of sterile PROTOPAM Chloride (pralidoxime chloride) for Injection white to off-white porous cake*, without diluent or syringe.

*When necessary, sodium hydroxide is added during processing to adjust the pH.

Storage

Store at 20°-25°C (68°-77°F), excursions permitted to 15°-30°C (59°-86°F) [see USP Controlled Room Temperature].

ANIMAL PHARMACOLOGY AND TOXICOLOGY

The following table lists chemical and trade or generic names of pesticides, chemicals, and drugs against which PROTOPAM Chloride (usually administered in conjunction with atropine) has been found to have antidotal activity on the basis of animal experiments. All compounds listed are organophosphates having anticholinesterase activity. A great many additional substances are in industrial use but have been omitted because of lack of specific information.

AAT—see PARATHION
AFLIX—see FORMOTHION
ALKRON—see PARATHION
AMERICAN CYANAMID 3422—see PARATHION
AMITON—diethyl-S-(2-diethylaminoethyl)phosphorothiolate
ANTHIO—see FORMOTHION
APHAMITE—see PARATHION
ARMIN—ethyl-4-nitrophenylethylphosphonate
AZINPHOS-METHYL—dimethyl-S-[(4-oxo-1,2,3,-benzotriazin-3(4 H)-yl)methyl] phosphorodithioate
MORPHOTHION—dimethyl-S-2-keto-2-(N-morpholyl)ethylphosphorodithioate
NEGUVON—see TRICHLOROFON
NIRAN—see PARATHION
NITROSTIGMINE—see PARATHION
O,O-DIETHYL-O-p-NITROPHENYL PHOSPHOROTHIOATE—see PARATHION
O,O-DIETHYL-O-p-NITROPHENYLTHIO PHOSPHATE—see PARATHION
OR 1191—see PHOSPHAMIDON
OS 1836—see VINYLPHOS
OXYDEMETONMETHYL—dimethyl-S-2-(ethylsulfinyl) ethyl phosphorothiolate
PARAOXON—diethyl (4-nitrophenyl) phosphate
PARATHION—diethyl (4-nitrophenyl) phosphorothionate
PENPHOS—see PARATHION
PHENCAPTON—diethyl-S-(2,5-dichlorophenylmercaptomethyl) phosphorodithioate
PHOSDRIN—see MEVINPHOS
PHOS-KIL—see PARATHION
PHOSPHAMIDON—1-chloro-1-diethylcarbamoyl-1-propen-2-yl-dimethylphosphate
PHOSPHOLINE IODIDE—see echothiophate iodide
PHOSPHOROTHIOIC ACID, O,O-DIETHYL-O-p-NITROPHENYL ESTER—see PARATHION
PLANTHION—see PARATHION
QUELETOX—see FENTHION
RH—see PARATHION
RU—4-tert-butyl-2-chlorophenylmethyl-N-methylphosphoroamidate
SARIN—isopropyl-methylphosphonofluoridate
SHELL OS 1836—see VINYLPHOS
SHELL 2046—see MEVINPHOS
SNP—see PARATHION
SOMAN - pinacolyl-methylphosphonofluoridate
SYSTOX - diethyl-(2-ethylmercaptoethyl) phosphorothionate
TEP - see TEPP
TEPP - tetraethylpyro phosphate
THIOPHOS- see PARATHION
TIGUVON - see FENTHION
TRICHLOROFON - dimethyl-1-hydroxy-2,2,2-trichloroethylphosphonate
VAPONA - see DICHLORVOS
VAPOPHOS - see PARATHION
VINYLPHOS - diethyl-2-chloro-vinylphosphate

PROTOPAM Chloride (pralidoxime chloride) appears to be ineffective, or marginally
effective, against poisoning by:

CIODRIN (alpha-methylbenzyl-3-[dimethoxyphosphinyloxy]-ciscrotonate)
DIMEFOX (tetramethylphosphorodiamidic fluoride)
DIMETHOATE (dimethyl-S-[N-methylcarbamoylmethyl]phosphorodithioate)
METHYL DIAZINON (dimethyl-[2-isopropyl-4-methylpyrimidyl]-phosphorothionate)
METHYL PHENCAPTON (dimethyl-S-[2,5-dichlorophenylmercaptomethyl]phosphorodithioate)
PHORATE (diethyl-S-ethylmercaptomethylphosphorodithioate)
SCHRADAN (octamethylpyrophosphoramide)
WEPSYN (5-amino-1-[bis-(dimethylamino) phosphinyl]-3-phenyl-1,2,4-triazole).

Baxter and Protopam are trademarks of Baxter International Inc.
All other trademarks or brand names appearing herein are the property of their respective owners.

Manufactured for
Baxter Healthcare Corporation
Deerfield, IL 60015 USA
By: Baxter Pharmaceutical Solutions LLC Bloomington, IN 47403

For Product Inquiry 1 800 ANA DRUG (1-800-262-3784)

07-19-00-0141

Rev: January 2018

PACKAGE LABEL - Principal Display Panel

Container Label

Container Label

NDC 60977-141-27

Protopam Chloride

(pralidoxime chloride) for injection

1 g Single Dose Vial

Rx only

FOR INTRAVENOUS INJECTION;

may be given subcutaneously or

intramuscularly if this route is not feasible.

Prepare injection by adding

20 mL of Sterile Water for

Injection, USP.

Usual Dosage: 1 g

See accompanying descriptive

literature. Discard unused solution

after a dose have been withdrawn.

Prepared by cryodesiccation.

esi

Mfd. for Baxter Healthcare Corp.

Deerfield, IL 60015 USA

by: Baxter Pharmaceutical Solutions, LLC

Bloomington, IN 47403

460-496-01

(01)00360977141275

3-942-233

Lot:

Exp:

Carton Label

Carton Label

NDC 60977-141-01

Protopam Chloride

(pralidoxime chloride) for injection

1 g

Rx only

6 x 1 g Single Dose Vials

FOR INTRAVENOUS INJECION;

may also be given by intramuscular or subcutaneous

injection if the intravenous route is not feasible.

esi

Manufactured for

Baxter Healthcare Corporation

Deerfield, IL 60015 USA

by: Baxter Pharmaceutical Solutions, LLC

Bloomington, IN 47403

Lot:

Exp:

NDC 60977-141-01

Protopam Chloride

(pralidoxime chloride) for injection

1 g

6 x 1 g Single Dose Vials

N3 60977 14101 5

Enclosed in this package are six vials, each containing 1 g of sterile

Protopam Chloride (pralidoxime chloride). When necessary, either 1N

hydrochloric acid or 1N sodium hydroxide may be added during

processing to adjust the pH. Prepare injection by adding 20 mL of

Sterile Water for Injection, USP (not supplied in this package).

Usual Dosage: 1 g

See accompanying descriptive literature.

Discard unused solution after a dose has been withdrawn.

Prepared by cryodesiccation.

Enclosed product circular for human use.

Store at 20°-25°C (68°-77°F) [see USP Controlled Room Temperature].

Baxter and Protopam are trademarks of Baxter International Inc. or its subsidiaries.

460-497-00

3-809-1808

NDC 60977-141-01

Protopam Chloride

(pralidoxime chloride) for injection

1 g

6 x 1 g Single Dose Vials

FOR INTRAVENOUS INJECTION;

may also be given by intramuscular

or subcutaneous injection

if the intravenous route is not feasible.

esi

Manufactured for

Baxter Healthcare Corporation

Deerfield, IL 60015 USA

by: Baxter Pharmaceutical Solutions LLC

Bloomington, IN 47403